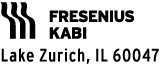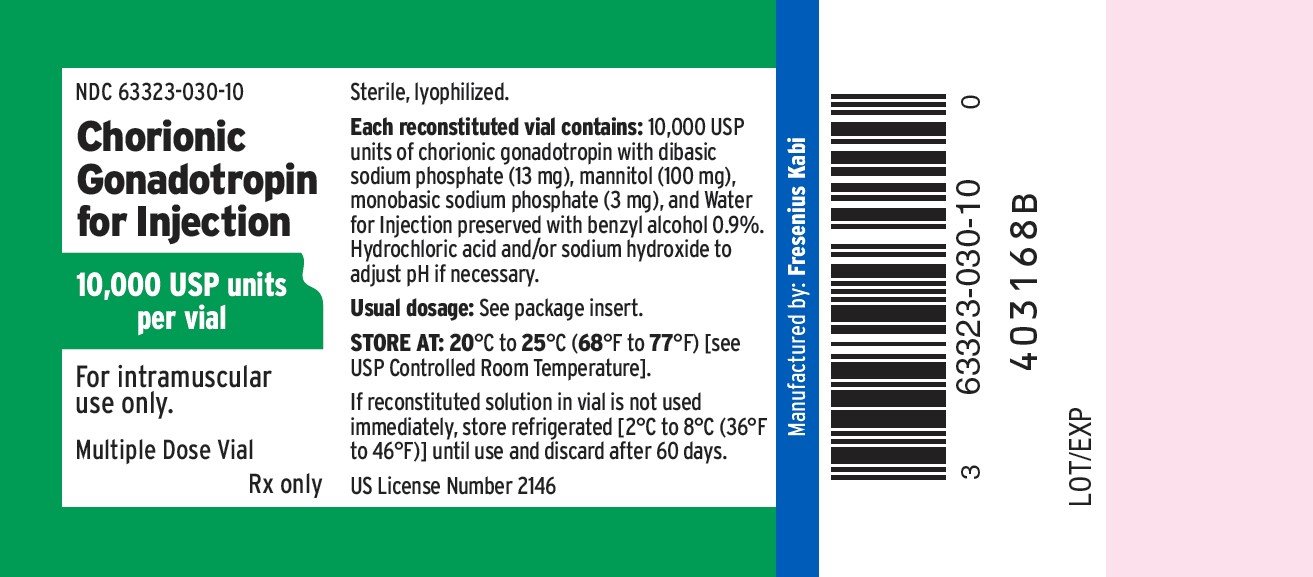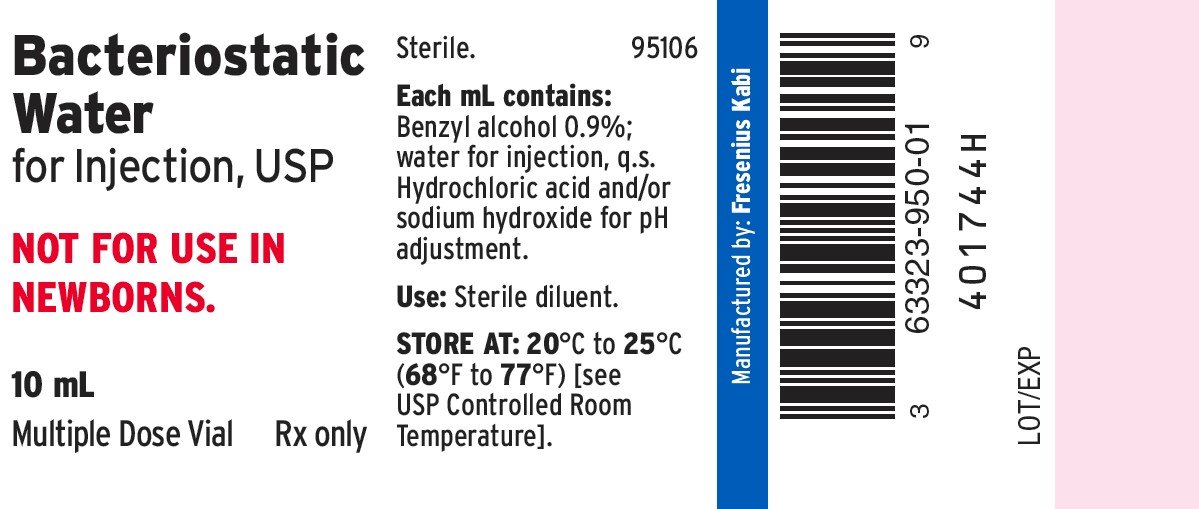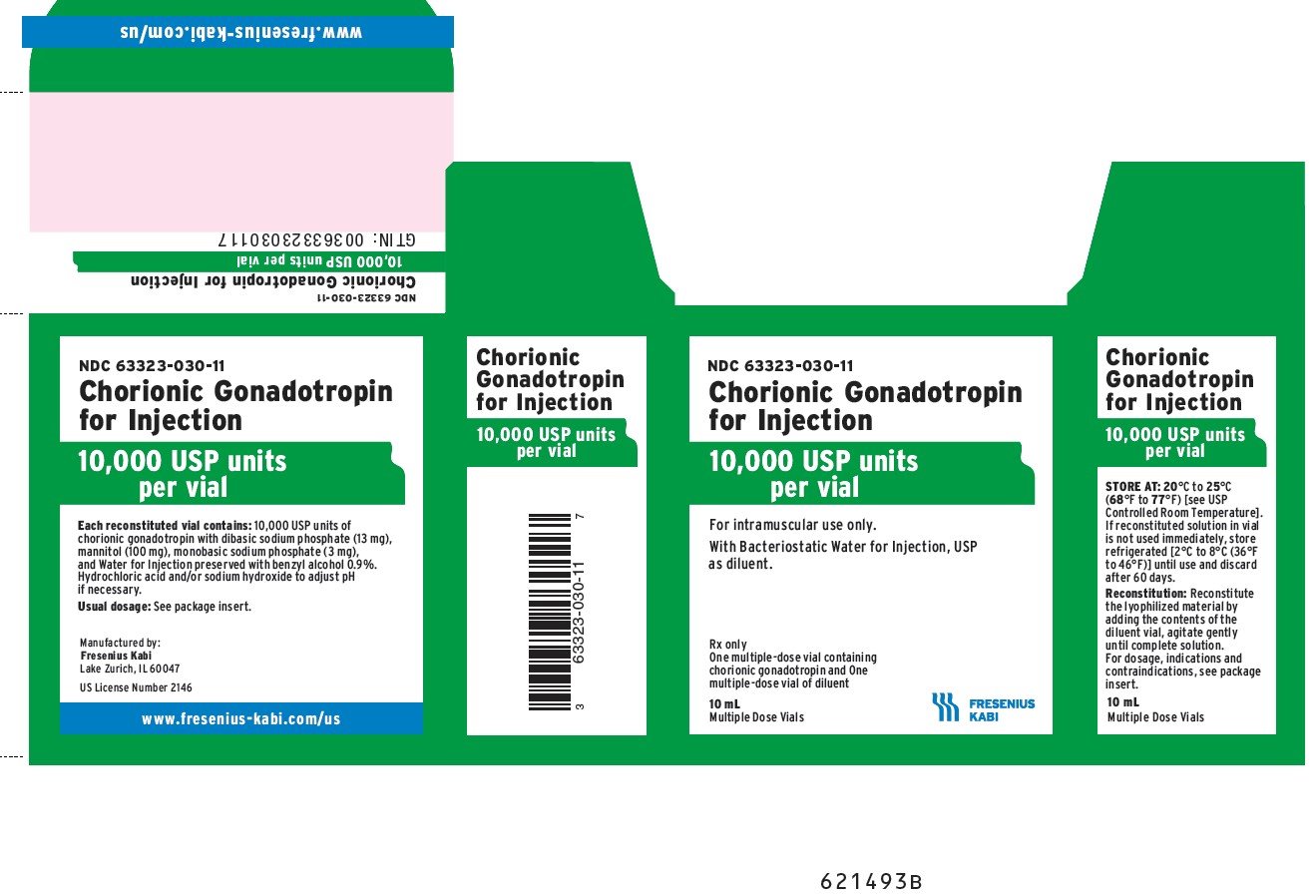 DRUG LABEL: Chorionic Gonadotropin
NDC: 63323-030 | Form: KIT | Route: INTRAMUSCULAR
Manufacturer: Fresenius Kabi USA, LLC
Category: prescription | Type: HUMAN PRESCRIPTION DRUG LABEL
Date: 20250411

ACTIVE INGREDIENTS: CHORIOGONADOTROPIN ALFA 10000 [USP'U]/10 mL
INACTIVE INGREDIENTS: MANNITOL; BENZYL ALCOHOL; SODIUM PHOSPHATE, DIBASIC, UNSPECIFIED FORM; SODIUM PHOSPHATE, MONOBASIC, UNSPECIFIED FORM; SODIUM HYDROXIDE; HYDROCHLORIC ACID; HYDROCHLORIC ACID; WATER; BENZYL ALCOHOL; SODIUM HYDROXIDE

Chorionic Gonadotropin

Rx only

DESCRIPTION:

Human chorionic gonadotropin (HCG), a polypeptide hormone produced by the human placenta, is composed of an alpha and a beta sub-unit. The alpha sub-unit is essentially identical to the alpha sub-units of the human pituitary gonadotropins, luteinizing hormone (LH) and follicle-stimulating hormone (FSH), as well as to the alpha sub-unit of human thyroid-stimulating hormone (TSH). The beta sub-units of these hormones differ in amino acid sequence. Chorionic gonadotropin is obtained from the human pregnancy urine. It is standardized by a biological assay procedure.

Chorionic Gonadotropin for injection is a sterile lyophilized powder available in multiple dose vials containing 10,000 USP units to be reconstituted with accompanying Bacteriostatic Water for Injection and administered intramuscularly after reconstitution. When reconstituted with 10 mL of the accompanying diluent each vial contains:

Chorionic gonadotropin 10,000 USP units

benzyl alcohol 0.9%

dibasic sodium phosphate 13 mg

mannitol 100 mg

monobasic sodium phosphate 3 mg

water for injection q.s.

Buffered with dibasic sodium phosphate and monobasic sodium phosphate. Hydrochloric acid and/or sodium hydroxide may have been used for pH adjustment (6.0-8.0). Nitrogen gas is used in the freeze drying process.

CLINICAL PHARMACOLOGY:

The action of HCG is virtually identical to that of pituitary LH, although HCG appears to have a small degree of FSH activity as well. It stimulates production of gonadal steroid hormones by stimulating the interstitial cells (Leydig cells) of the testis to produce androgens and the corpus luteum of the ovary to produce progesterone. Androgen stimulation in the male leads to the development of secondary sex characteristics and may stimulate testicular descent when no anatomical impediment to descent is present. This descent is usually reversible when HCG is discontinued. During the normal menstrual cycle, LH participates with FSH in the development and maturation of the normal ovarian follicle, and the mid-cycle LH surge triggers ovulation. HCG can substitute for LH in this function. During a normal pregnancy, HCG secreted by the placenta maintains the corpus luteum after LH secretion decreases, supporting continued secretion of estrogen and progesterone and preventing menstruation. HCG HAS NO KNOWN EFFECT ON FAT MOBILIZATION, APPETITE OR SENSE OF HUNGER, OR BODY FAT DISTRIBUTION.

INDICATIONS AND USAGE:

HCG HAS NOT BEEN DEMONSTRATED TO BE EFFECTIVE ADJUNCTIVE THERAPY IN THE TREATMENT OF OBESITY. THERE IS NO SUBSTANTIAL EVIDENCE THAT IT INCREASES WEIGHT LOSS BEYOND THAT RESULTING FROM CALORIC RESTRICTION, THAT IT CAUSES A MORE ATTRACTIVE OR ‘‘NORMAL’’ DISTRIBUTION OF FAT, OR THAT IT DECREASES THE HUNGER AND DISCOMFORT ASSOCIATED WITH CALORIE-RESTRICTED DIETS.

1. Prepubertal cryptorchidism not due to anatomical obstruction. In general, HCG is thought to induce testicular descent in situations when descent would have occurred at puberty. HCG thus may help predict whether or not orchiopexy will be needed in the future. Although, in some cases, descent following HCG administration is permanent, in most cases, the response is temporary. Therapy is usually instituted between the ages four and nine.
2. Selected cases of hypogonadotropic hypogonadism (hypogonadism secondary to a pituitary deficiency) in males.
3. Induction of ovulation and pregnancy in the anovulatory, infertile woman in whom the cause of anovulation is secondary and not due to primary ovarian failure, and who has been appropriately pretreated with human menotropins.

CONTRAINDICATIONS:

Precocious puberty, prostatic carcinoma or other androgen-dependent neoplasm, prior allergic reaction to HCG.

WARNINGS:

HCG should be used in conjunction with human menopausal gonadotropins only by physicians experienced with infertility problems who are familiar with the criteria for patient selection, contraindications, warnings, precautions and adverse reactions described in the package insert for menotropins. The principal serious adverse reactions are: (1) Ovarian hyperstimulation, a syndrome of sudden ovarian enlargement, ascites with or without pain and/or pleural effusion, (2) Rupture of ovarian cysts with resultant hemoperitoneum, (3) Multiple births and (4) Arterial thromboembolism.

Anaphylaxis and other hypersensitivity reactions have been reported with urinary-derived HCG products.

PRECAUTIONS:

General

Induction of androgen secretion by HCG may induce precocious puberty in patients treated for cryptorchidism. Therapy should be discontinued if signs of precocious puberty occur.

Since androgens may cause fluid retention, HCG should be used with caution in patients with cardiac or renal disease, epilepsy, migraine or asthma.

Drug/Laboratory Test Interactions

Chorionic gonadotropin may interfere with radioimmunoassay for gonadotropins, particularly luteinizing hormone.

Carcinogenesis, Mutagenesis, Impairment of Fertility

Long-term studies in animals have not been performed to evaluate the carcinogenic or mutagenic potential of chorionic gonadotropin.

Pediatric Use

Safety and effectiveness of chorionic gonadotropin in children below the age of four have not been established.

Pregnancy

TERATOGENIC EFFECTS

Teratogenic Effects: Chorionic gonadotropin may cause fetal harm when administered to a pregnant woman. Defects of forelimbs and central nervous system and alterations in sex ratio have been reported in mice receiving combined gonadotropin and chorionic gonadotropin therapy in dosages to induce superovulation. Multiple ovulations with resulting plural gestations (mostly twins) have been reported to occur in approximately 20% of pregnancies when conception has followed chorionic gonadotropin therapy.

Nursing Mothers

It is not known whether chorionic gonadotropin is excreted in human milk. Because many drugs are excreted in human milk, caution should be exercised when chorionic gonadotropin is administered to a nursing woman.

ADVERSE REACTIONS:

Headache, irritability, restlessness, depression, fatigue, edema, precocious puberty, gynecomastia and pain at the site of injection.

DOSAGE AND ADMINISTRATION:

Intramuscular Use Only

The dosage regimen employed in any particular case will depend upon the indication for use, the age and weight of the patient and the physician’s preference. The following regimens have been advocated by various authorities.

Prepubertal Cryptorchidism Not Due To Anatomical Obstruction

1. 4,000 USP units three times weekly for three weeks.
2. 5,000 USP units every second day for four injections.
3. 15 injections of 500 to 1,000 USP units over a period of six weeks.
4. 500 USP units three times weekly for four to six weeks. If this course of treatment is not successful, another is begun one month later giving 1,000 USP units per injection.

Selected Cases Of Hypogonadotropic Hypogonadism In Males

1. 500 to 1,000 USP units three times a week for three weeks, followed by the same dose twice a week for three weeks.
2. 4,000 USP units three times weekly for six to nine months, following which the dosage may be reduced to 2,000 USP units three times weekly for an additional three months.

Induction of ovulation and pregnancy in the anovulatory, infertile woman in whom the cause of anovulation is secondary and not due to primary ovarian failure and who has been appropriately pretreated with human menotropins (see prescribing information for menotropins for dosage and administration for that drug product). 5,000 to 10,000 USP units one day following the last dose of menotropins. (A dosage of 10,000 USP units is recommended in the labeling for menotropins.)

IMPORTANT: USE COMPLETELY WITHIN 60 DAYS AFTER RECONSTITUTION. REFRIGERATE AFTER RECONSTITUTION.

DIRECTIONS FOR RECONSTITUTION:

Two-Vial Package

Withdraw sterile air from lyophilized vial and inject into diluent vial. Remove 10 mL from diluent vial and add to lyophilized vial; agitate gently until solution is complete.

HOW SUPPLIED:

Chorionic Gonadotropin, lyophilized powder, is supplied in two-vial packages including Bacteriostatic Water for Injection as diluent as follows:

Product Code | Unit of Sale | Description
325011 | NDC 63323-030-11 | One carton containing Chorionic Gonadotropin, 10,000 USP units per vial in a 10 mL multiple dose vial (NDC 63323-030-10) with accompanying diluent (NDC 63323-950-01).

Store at room temperature 20°C to 25°C (68°F to 77°F) [see USP Controlled Room Temperature]. If needed, the reconstituted vial may be refrigerated between 2℃ to 8℃ (36℉ to 46℉) and must be discarded after 60 days. Do not freeze and do not shake.

Manufactured by:

www.fresenius-kabi.com/us

US License Number 2146

45792J

Revised: February 2025

PACKAGE LABEL – PRINCIPAL DISPLAY – Chorionic Gonadotropin 10 mL Multiple Dose Vial Label

NDC 63323-030-10

Chorionic

Gonadotropin

for Injection

10,000 USP units

per vial

For intramuscular

use only.

Multiple Dose Vial

Rx only

PACKAGE LABEL - PRINCIPAL DISPLAY - Bacteriostatic Water 10 mL Multiple Dose Vial Label

Bacteriostatic

Water

for Injection, USP

NOT FOR USE IN

NEWBORNS.

10 mL

Multiple Dose Vial Rx only

PACKAGE LABEL – PRINCIPAL DISPLAY – Chorionic Gonadotropin 10 mL Multiple Dose Vial Carton Panel

NDC 63323-030-11

Chorionic Gonadotropin

for Injection

10,000 USP units

per vial

For intramuscular use only.

With Bacteriostatic Water for Injection, USP

as diluent.

Rx only

One multiple-dose vial containing

chorionic gonadotropin and One

multiple-dose vial of diluent

10 mL

Multiple Dose Vials